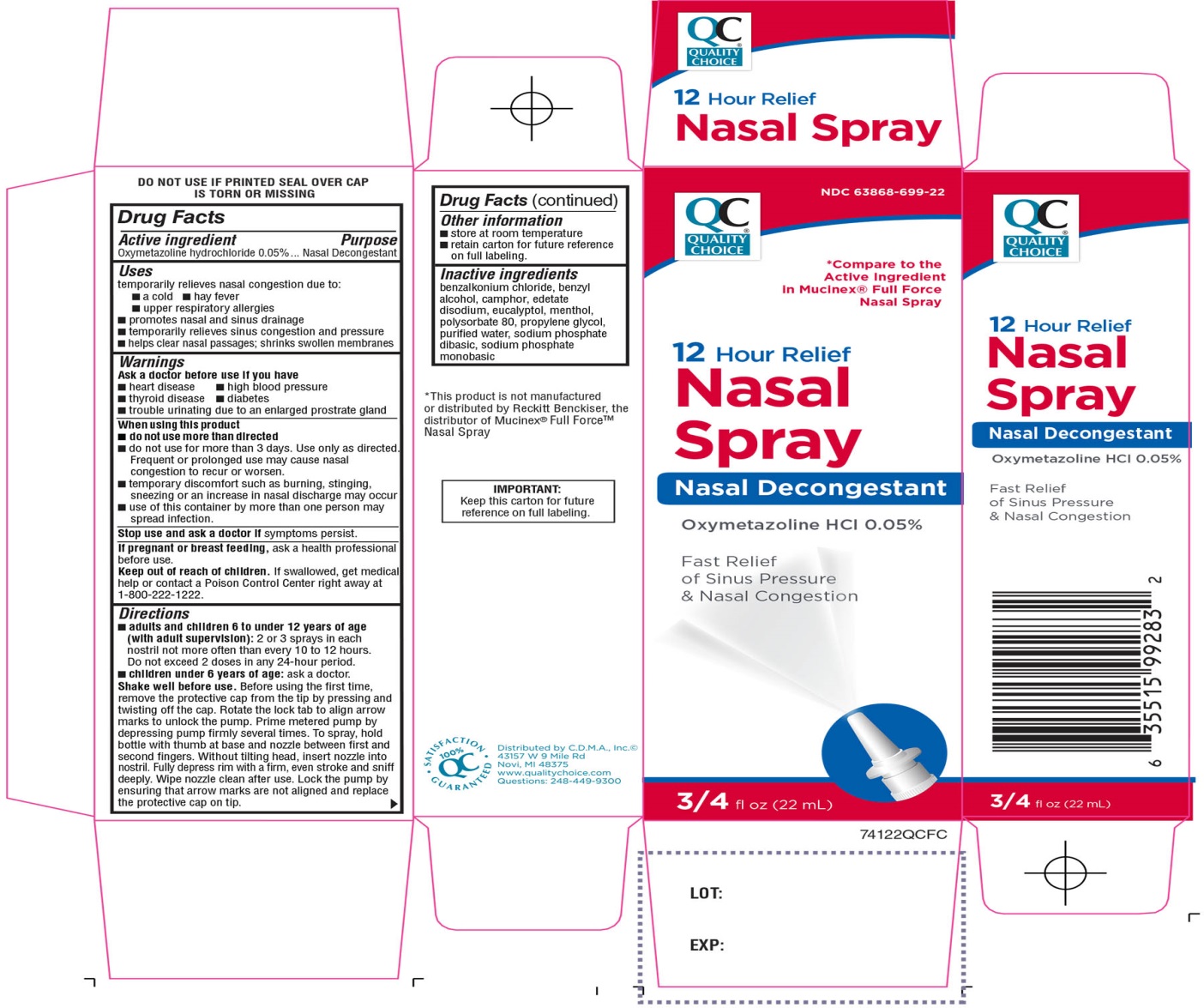 DRUG LABEL: Quality Choice
NDC: 63868-699 | Form: SPRAY
Manufacturer: CHAIN DRUG MARKETING ASSOCIATION
Category: otc | Type: HUMAN OTC DRUG LABEL
Date: 20251204

ACTIVE INGREDIENTS: OXYMETAZOLINE HYDROCHLORIDE 0.05 g/100 mL
INACTIVE INGREDIENTS: BENZALKONIUM CHLORIDE; BENZYL ALCOHOL; CAMPHOR (NATURAL); EDETATE DISODIUM; EUCALYPTOL; MENTHOL, UNSPECIFIED FORM; POLYSORBATE 80; PROPYLENE GLYCOL; WATER; SODIUM PHOSPHATE, DIBASIC, UNSPECIFIED FORM; SODIUM PHOSPHATE, MONOBASIC, UNSPECIFIED FORM

Quality Choice 12 Hour Relief Nasal Spray Drug Facts

Active ingredient

Oxymetazoline hydrochloride 0.05%

Purpose

Nasal Decongestant

Uses

temporarily relieves nasal congestion due to:

- a cold
- hay fever
- upper respiratory allergies
- promotes nasal and sinus drainage
- temporarily relieves sinus congestion and pressure
- helps clear nasal passages; shrinks swollen nasal membranes

Ask a doctor before use if you have

- heart disease
- high blood pressure
- thyroid disease
- diabetes
- trouble urinating due to an enlarged prostate gland

When using this product

- do not use more than directed
- do not use for more than 3 days. Use only as directed. Frequent or prolonged use may cause nasal congestion to recur or worsen.
- temporary discomfort such as burning, stinging, sneezing or an increase in nasal discharge may occur
- use of this container by more than one person may spread infection

Stop use and ask a doctor if

symptoms persist

If pregnant or breast-feeding,

ask a health professional before use.

Keep out of reach of children.

If swallowed, get medical help or contact a Poison Control Center right away (1-800-222-1222).

Directions

- adults and children 6 to under 12 years of age (with adult supervision):2 or 3 sprays in each nostril not more often than every 10 to 12 hours. Do not exceed 2 doses in any 24-hour period.
- children under 6 years of age:ask a doctor

Shake well before use:Before using the first time, remove the protective cap from the tip by pressing and twisting off the cap.

Rotate the lock tab to align arrow marks to unlock the pump. Prime the lock tab to align arrow marks to unlock the pump. Prime metered pump by depressing pump firmly several times.

To spray, hold bottle with thump at base and nozzle between first and second fingers. Without tilting head, insert nozzle into nostril. Fully depress rim with a firm, even stroke and sniff deeply.

Wipe nozzle clean after use. Lock the pump by ensuring that arrow marks are not aligned and replace the protective cap on tip.

Other information

- store at room temperature
- retain carton for future reference on full labeling

Inactive ingredients

benzalkonium chloride, benzyl alcohol, camphor, edetate disodium, eucalyptol, menthol, polysorbate 80, propylene glycol, purified water, sodium phosphate dibasic, sodium phosphate monobasic.

Questions or comments?

1-866-467-2748

Principal Display Panel

NDC# 63868-699-22

QUALITY CHOICE®

* Compare to Active Ingredient in Mucinex® Full Force Nasal Spray

12 Hour Relief

Nasal Spray

Nasal Decongestant

Oxymetazoline HCl 0.05%

Fast Relief of Sinus Pressure & Nasal Congestion

3/4 FL OZ (22 mL)

100% QC SATISFACTION GUARANTEED

Distributed by C.D.M.A. Inc. ©

43157 W 9 Mile Rd

Novi, MI 48375

www.qualitychoice.com

Questions: 248-449-9300

*This product is not manufactured or distributed by Reckitt Benckiser, the distributor of Mucinex®Full Force™ Nasal Spray.